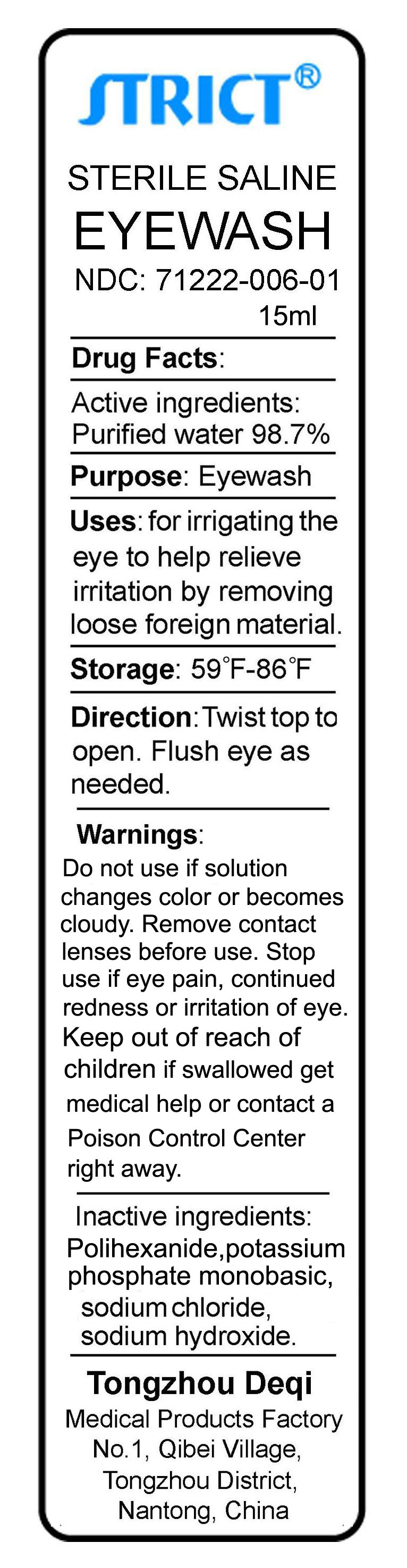 DRUG LABEL: Sterile Saline Eyewash
NDC: 71222-006 | Form: SOLUTION
Manufacturer: Tongzhou  Deqi  Medical  Products  Factory
Category: otc | Type: HUMAN OTC DRUG LABEL
Date: 20170601

ACTIVE INGREDIENTS: WATER 0.987 mL/1 mL
INACTIVE INGREDIENTS: POLIHEXANIDE; SODIUM CHLORIDE; POTASSIUM PHOSPHATE, MONOBASIC; SODIUM HYDROXIDE

Drug Fact

Active Ingredient

water 98.7%

Purpose

eyewash

Warnings

Do not use if solution changes color or becomes cloudy.remove contact lenses before use.stop use if eye pain continued redness or irritation of eye .

Keep out of reach of children.in case of axxidental ingestion,seek professional assistance or consult a poison control center immediately.

Directions

Twist top to open,Flush eye as needed.

Use

for irrigating the eye to help relieve irritation by removeing loose foreign material.

Inactive Ingredients

Sodium chloride ,Potassium phosphate monobasic ,Sodium hydroxide,POLIHEXANIDE